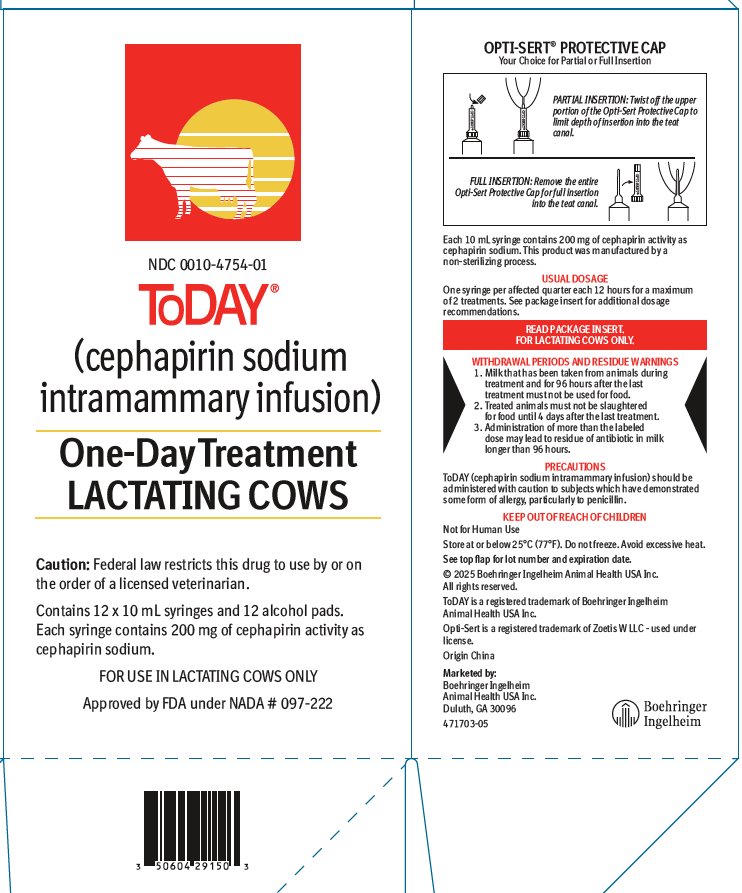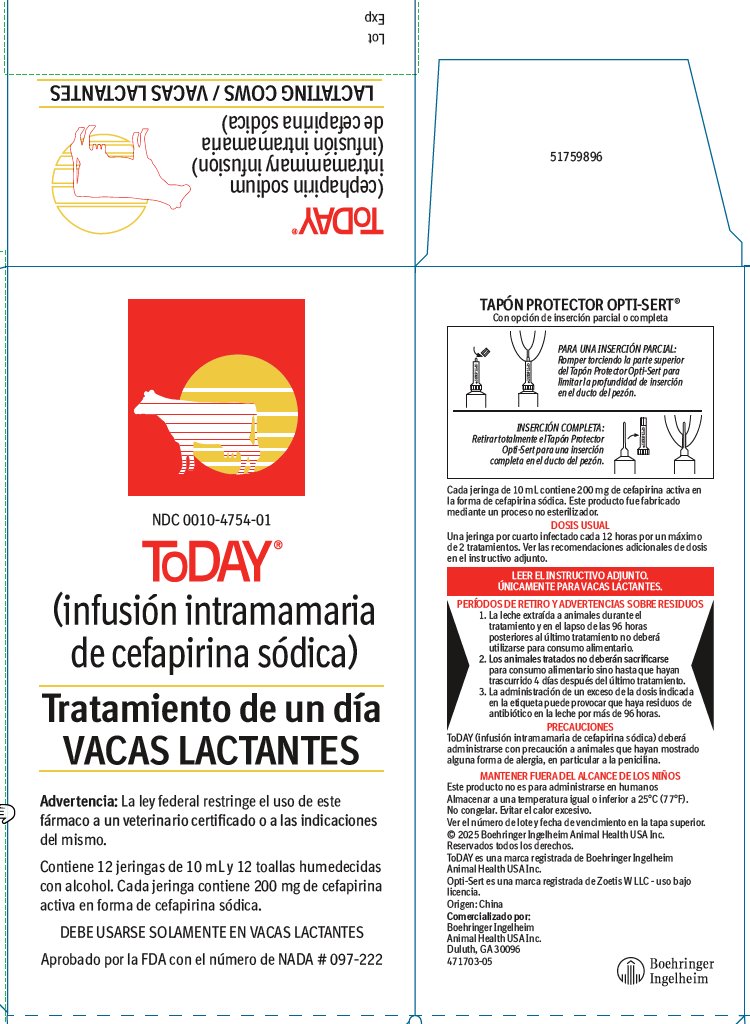 DRUG LABEL: ToDAY
NDC: 0010-4754 | Form: SUSPENSION
Manufacturer: Boehringer Ingelheim Animal Health USA Inc.
Category: animal | Type: PRESCRIPTION ANIMAL DRUG LABEL
Date: 20251223

ACTIVE INGREDIENTS: cephapirin sodium 200 mg/10 mL

ToDAY®
(cephapirin sodium intramammary infusion)
(infusión intramamaria decefapirina sódica)

FOR USE IN LACTATING COWS ONLY
DEBE USARSE SOLAMENTE EN VACAS LACTANTES

Approved by FDA under NADA # 097-222

Aprobado por la FDA con el número de NADA # 097-222

Caution: Federal law restricts this drug to use by or on the order of a licensed veterinarian.

Advertencia: La ley federal restringe el uso de este fármaco a un veterinario certificado o a las indicaciones del mismo.

DESCRIPTION

ToDAY (cephapirin sodium intramammary infusion) is a cephalosporin which possesses a wide range of antimicrobial activity against gram-positive and gram-negative organisms. It is derived biosynthetically from 7-aminocephalosporanic acid.

Each 10 mL disposable syringe contains 200 mg of cephapirin activity in a stable peanut oil gel. This product was manufactured by a non-sterilizing process.

Store at or below 25°C (77°F). Do not freeze. Avoid excessive heat.

DESCRIPCIÓN

ToDAY (infusión intramamaria de cefapirina sódica) es una cefalosporina que posee un amplio espectro de actividad antimicrobiana contra organismos grampositivos y gramnegativos. El producto es un derivado biosintético del ácido 7-aminocefalosporánico.

Cada jeringa desechable de 10 mL contiene 200 mg de cefapirina activa en un gel estable de aceite de maní (cacahuate). Este producto fue fabricado mediante un proceso no esterilizador.

Almacenar a una temperatura igual o inferior a 25ºC (77ºF). No congelar. Evitar el calor excesivo.

ACTION

Cephapirin is bactericidal to susceptible organisms; it is known to be highly active against Streptococcus agalactiae and Staphylococcus aureus including strains resistant to penicillin.

To determine the susceptibility of bacteria to cephapirin in the laboratory, the class disc, Cephalothin Susceptibility Test Discs, 30 mcg, should be used.

ACCIÓN

La cefapirina tiene una acción bactericida contra organismos susceptibles; se sabe que es extremadamente activa contra el Streptococcus agalactiae y el Staphylococcus aureus, incluyendo cepas resistentes a la penicilina.

Para determinar en laboratorio la susceptibilidad de las bacterias a la cefapirina deberá utilizarse el disco de clase, Discos de Prueba de Susceptibilidad a la Cefalotina, 30 mcg.

INDICATIONS

FOR LACTATING COWS ONLY / For the Treatment of Bovine Mastitis

ToDAY (cephapirin sodium intramammary infusion) should be used at the first signs of inflammation or at the first indication of any alteration in the milk. Treatment is indicated immediately upon determining, by C.M.T. or other tests, that the leukocyte count is elevated, or that a susceptible pathogen has been cultured from the milk.

ToDAY has been shown to be efficacious in the treatment of mastitis in lactating cows caused by susceptible strains of Streptococcus agalactiae and Staphylococcus aureus including strains resistant to penicillin.

INDICACIONES

ÚNICAMENTE PARA VACAS LACTANTES / Para el tratamiento de mastitis bovina

ToDAY (infusión intramamaria de cefapirina sódica) debe utilizarse ante los primeros signos de inflamación o ante el primer indicio de cualquier alteración en la leche. El tratamiento resulta indicado inmediatamente después de determinar mediante la prueba de California para mastitis (C.M.T.) u otras pruebas, que el conteo de leucocitos resulta elevado o cuando algún patógeno susceptible haya sido cultivado a partir de la leche.

Se ha demostrado que ToDAY es eficaz en el tratamiento de la mastitis en vacas lactantes causada por cepas susceptibles de Streptococcus agalactiae y Staphylococcus aureus, incluidas cepas resistentes a la penicilina.

DOSAGE AND DIRECTIONS FOR USE

Infuse the entire contents of one syringe (10 mL) into each infected quarter immediately after the quarter has been completely milked out. Repeat once only in 12 hours. If definite improvement is not noted within 48 hours after treatment, the causal organism should be further investigated. Consult your veterinarian.

Milk out udder completely. Wash the udder and teats thoroughly with warm water containing a suitable dairy antiseptic and dry, preferably using individual paper towels. Carefully scrub the teat end and orifice with 70% alcohol, using a separate swab for each teat. Allow to dry.

ToDAY (cephapirin sodium intramammary infusion) is packaged with the Opti-Sert® Protective Cap.

For partial insertion: Twist off upper portion of the Opti-Sert Protective Cap to expose 3–4 mm of the syringe tip.

For full insertion: Remove protective cap to expose the full length of the syringe tip.

Insert syringe tip into the teat canal and expel the entire contents of one syringe into each infected quarter. Withdraw the syringe and gently massage the quarter to distribute the suspension into the milk cistern. Do not milk out for 12 hours.

Do not infuse contents of the mastitis syringe into the teat canal if the Opti-Sert Protective Cap is broken or damaged.

Reinfection – The use of antibiotics, however effective, for the treatment of mastitis will not significantly reduce the incidence of this disease in the herd unless their use is fortified by good herd management, and sanitary and mechanical safety measures are practiced to prevent reinfection.

DOSIS E INSTRUCCIONES DE USO

Introducir por infusión todo el contenido de una jeringa (10 mL) en cada cuarto infectado inmediatamente después de haberlo ordeñado por completo. Repetir la operación una sola vez 12 horas después. En caso de no observar una mejoría notoria dentro de las 48 horas posteriores al tratamiento será necesario investigar más a fondo al organismo causal. Consulte a su médico veterinario.

Ordeñar completamente la ubre. Lavar la ubre y los pezones a fondo con agua tibia mezclada con un antiséptico adecuado para ganado lechero y secar utilizando de preferencia toallas de papel individuales. Con cuidado frotar la punta del pezón y el orificio con una solución de alcohol al 70%, empleando una torunda distinta para cada pezón. Dejar secar.

ToDAY (infusión intramamaria de cefapirina sódica) se envasa con la tapa protectora Opti-Sert®.

Para una inserción parcial: Romper torciendo la parte superior del Tapón Protector Opti-Sert para dejar expuestos de 3 a 4 mm de la punta de la jeringa.

Para una inserción completa: Retirar el tapón para exponer completamente la punta de la jeringa.

Insertar la punta de la jeringa en el ducto del pezón y expulsar todo el contenido de una jeringa dentro de cada cuarto infectado. Retirar la jeringa y masajear suavemente el cuarto para distribuir la suspensión en la cisterna de la leche. No ordeñar durante un lapso de 12 horas.

No introducir por infusión el contenido de la jeringa para tratar la mastitis en el ducto del pezón si el Tapón Protector Opti-Sert está roto o dañado.

Reinfección – No obstante su eficacia, el empleo de antibióticos para el tratamiento de mastitis no disminuirá significativamente la incidencia de esta enfermedad en el hato a menos que su empleo esté reforzado por un buen manejo del hato y siempre y cuando se practiquen medidas de seguridad sanitarias y mecánicas para prevenir la reinfección.

PRECAUTIONS

ToDAY should be administered with caution to subjects which have demonstrated some form of allergy, particularly to penicillin. Such reactions are rare; however, should they occur, consult your veterinarian.

PRECAUCIONES

ToDAY deberá administrarse con precaución a animales que hayan mostrado alguna forma de alergia, en particular a la penicilina. Estas reacciones son raras; sin embargo, en caso de que ocurrieran, habrá que consultar al médico veterinario.

WITHDRAWAL PERIODS AND RESIDUE WARNINGS

1. Milk that has been taken from animals during treatment and for 96 hours after the last treatment must not be used for food.
2. Treated animals must not be slaughtered for food until 4 days after the last treatment.
3. Administration of more than the labeled dose may lead to residue of antibiotic in milk longer than 96 hours.

PERÍODOS DE RETIRO Y ADVERTENCIAS SOBRE RESIDUOS

1. La leche extraída a animales durante el tratamiento y en el lapso de las 96 horas posteriores al último tratamiento no deberá utilizarse para consumo alimentario.

2. Los animales tratados no deberán sacrificarse para consumo alimentario sino hasta que hayan trascurrido 4 días después del último tratamiento.

3. La administración de un exceso de la dosis indicada en la etiqueta puede provocar que haya residuos de antibiótico en la leche por más de 96 horas.

CONTACT INFORMATION

For technical assistance or to report suspected adverse drug experiences, contact Boehringer Ingelheim Animal Health USA Inc. at 1-888-637-4251. For additional information about adverse drug experience reporting for animal drugs, contact FDA at 1-888-FDA-VETS or http://www.fda.gov/reportanimalae.

INFORMACIÓN DE CONTACTO

Para obtener asistencia técnica o para informar presuntas experiencias adversas con medicamentos, comuníquese con Boehringer Ingelheim Animal Health USA Inc. al 1-888-637-4251. Para obtener información adicional sobre la notificación de experiencias adversas con medicamentos para animales, comuníquese con la Administración de Alimentos y Medicamentos (Food and Drug Administration, FDA) al 1-888-FDA-VETS o en http://www.fda.gov/reportanimalae.

HOW SUPPLIED

ToDAY (cephapirin sodium intramammary infusion) is supplied in cartons containing 12 x 10 mL syringes with 12 convenient single use alcohol pads (NDC 0010-4754-01) and pails containing 144 x 10 mL syringes and 144 convenient single use alcohol pads (NDC 0010-4754-02).

FORMAS DE PRESENTACIÓN

ToDAY (infusión intramamaria de cefapirina sódica) se suministra en cajas que contienen 12 jeringas de 10 ml con 12 útiles almohadillas con alcohol para un solo uso (NDC 0010-4754-01) y en contenedores que contienen 144 jeringas de 10 ml y 144 útiles almohadillas con alcohol para un solo uso (NDC 0010-4754-02).

© 2025 Boehringer Ingelheim Animal Health USA Inc. All rights reserved.

ToDAY is a registered trademark of Boehringer Ingelheim Animal Health USA Inc.

Opti-Sert is a registered trademark of Zoetis W LLC - used under license.

Origin China

Marketed by:

Boehringer Ingelheim Animal Health USA Inc.

Duluth, GA 30096

471701-04 Revised 07/2025

51759899

© 2025 Boehringer Ingelheim Animal Health USA Inc. Reservados todos los derechos.

ToDAY es una marca registrada de Boehringer Ingelheim Animal Health USA Inc.

Opti-Sert es una marca registrada de Zoetis W LLC - uso bajo licencia.

Comercializado por: Boehringer Ingelheim Animal Health USA Inc.

Duluth, GA 30096

471701-04 Revised 07/2025

51759899 Origen: China